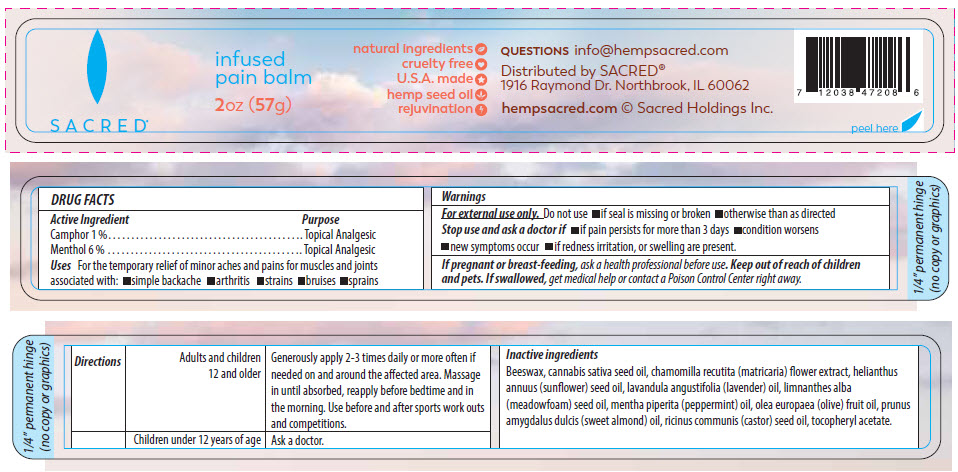 DRUG LABEL: Hemp Pain Balm 
NDC: 73616-208 | Form: OINTMENT
Manufacturer: Sacred Enterprises LLC
Category: otc | Type: HUMAN OTC DRUG LABEL
Date: 20200318

ACTIVE INGREDIENTS: .ALPHA.,.ALPHA.-DIBROMO-D-CAMPHOR 1 g/100 g; MENTHOL, UNSPECIFIED FORM 6 g/100 g
INACTIVE INGREDIENTS: YELLOW WAX; Cannabis Sativa Seed Oil; Matricaria Chamomilla Root; SUNFLOWER OIL; LAVENDER OIL; MEADOWFOAM SEED OIL; Mentha piperita; OLEA EUROPAEA (OLIVE) OIL UNSAPONIFIABLES; ALMOND OIL; CASTOR OIL; .ALPHA.-TOCOPHEROL ACETATE

Hemp Pain Balm
Sacred® Pain Balm

DRUG FACTS

ACTIVE INGREDIENT

Active Ingredient | Purpose
Camphor 1 % | Topical Analgesic
Menthol 6 % | Topical Analgesic

Uses

For the temporary relief of minor aches and pains for muscles and joints associated with:

- simple backache
- arthritis
- strains
- bruises
- sprains

Warnings

For external use only.

Do not use

- if seal is missing or broken
- otherwise than as directed

Stop use and ask a doctor if

- if pain persists for more than 3 days
- condition worsens
- new symptoms occur
- if redness irritation, or swelling are present.

PREGNANCY OR BREAST FEEDING

If pregnant or breast-feeding, ask a health professional before use.

Keep out of reach of children and pets. If swallowed, get medical help or contact a Poison Control Center right away.

DOSAGE AND ADMINISTRATION

Directions | Adults and children 12 and older | Generously apply 2-3 times daily or more often if needed on and around the affected area. Massage in until absorbed, reapply before bedtime and in the morning. Use before and after sports work outs and competitions.
 | Children under 12 years of age | Ask a doctor.

Inactive ingredients

Beeswax, cannabis sativa seed oil, chamomilla recutita (matricaria) flower extract, helianthus annuus (sunflower) seed oil, lavandula angustifolia (lavender) oil, limnanthes alba (meadowfoam) seed oil, mentha piperita (peppermint) oil, olea europaea (olive) fruit oil, prunus amygdalus dulcis (sweet almond) oil, ricinus communis (castor) seed oil, tocopheryl acetate.

QUESTIONS

info@hempsacred.com

Distributed by SACRED®
1916 Raymond Dr. Northbrook, IL 60062

PRINCIPAL DISPLAY PANEL - 57 g Jar Label

SACRED®

infused
pain balm

2oz (57g)